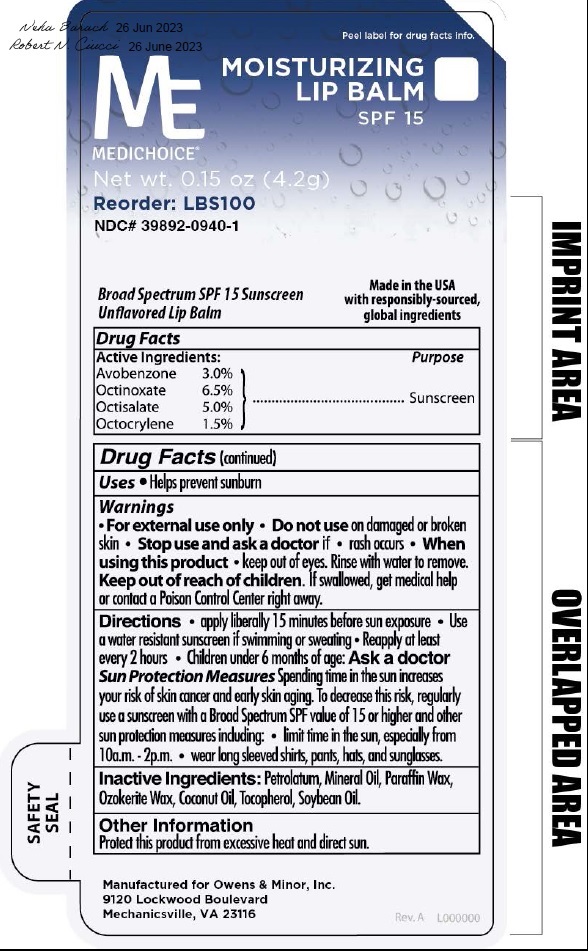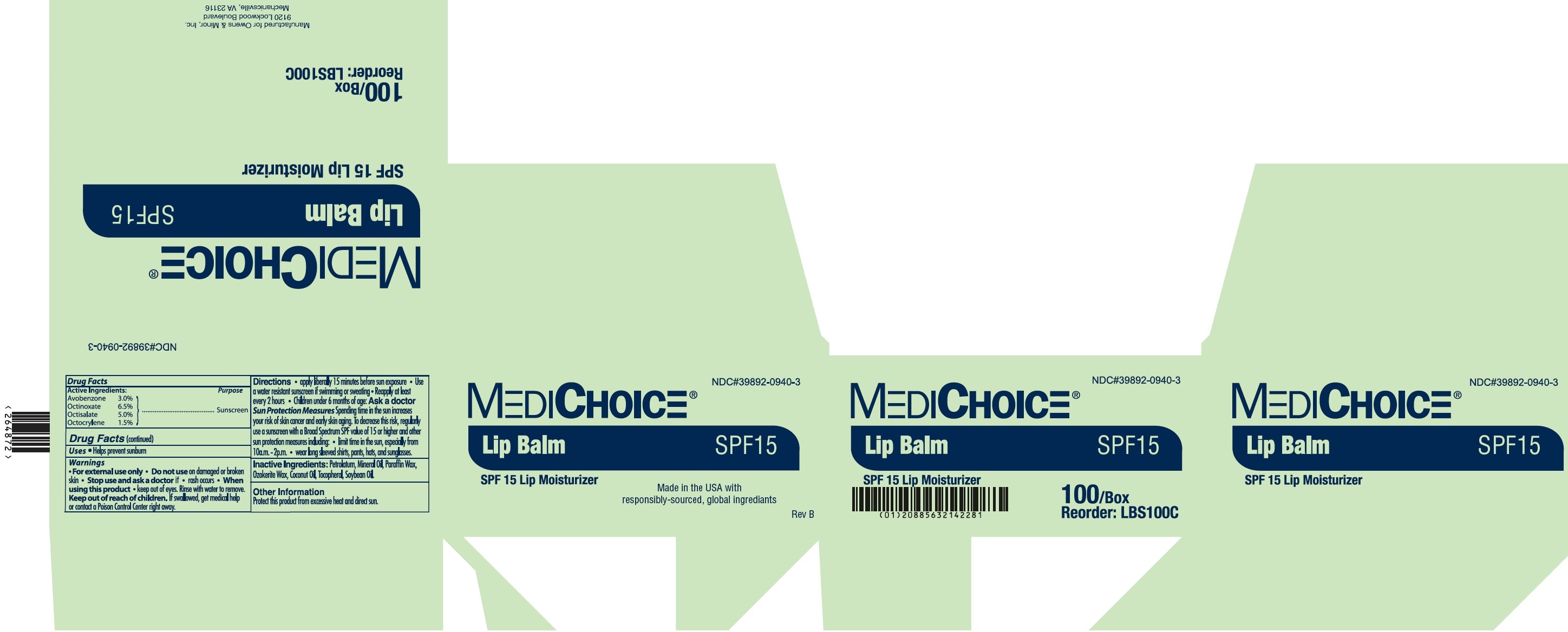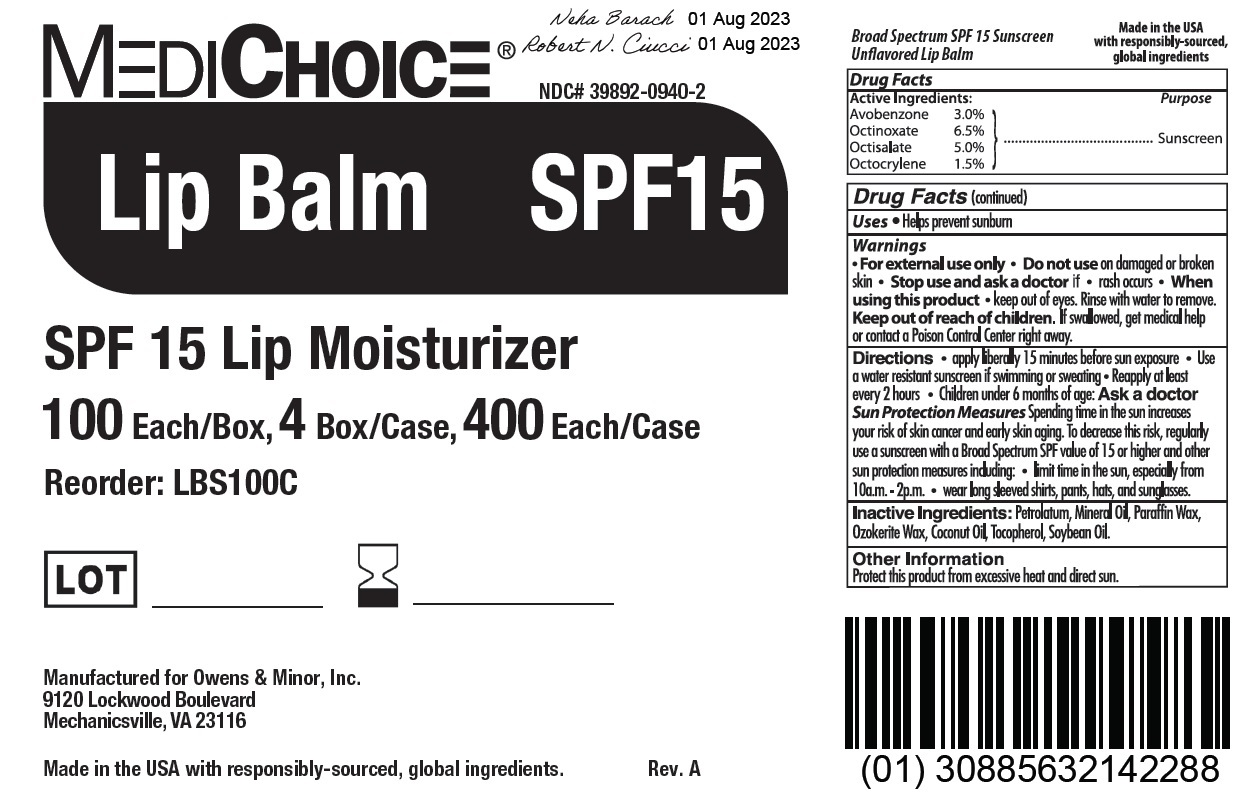 DRUG LABEL: MediChoice Moisturizing Lip Balm SPF15
NDC: 39892-0940 | Form: CREAM
Manufacturer: O&M HALYARD, INC.
Category: otc | Type: HUMAN OTC DRUG LABEL
Date: 20251009

ACTIVE INGREDIENTS: AVOBENZONE 30 mg/1 g; OCTINOXATE 65 mg/1 g; OCTISALATE 50 mg/1 g; OCTOCRYLENE 15 mg/1 g
INACTIVE INGREDIENTS: PETROLATUM; MINERAL OIL; PARAFFIN; CERESIN; COCONUT OIL; TOCOPHEROL; SOYBEAN OIL

MediChoice Moisturizing Lip Balm SPF15

Active Ingredients:

Avobenzone 3.0%

Octinoxate 6.5%

Octisalate 5.0%

Octocrylene 1.5%

Purpose

Sunscreen

Uses

- Helps prevent sunburn

Warnings

- For external use only

Do not use

- on damaged or broken skin

Stop use and ask a doctor if

- rash occurs

When using this product

- keep out of eyes. Rinse with water to remove.

Keep out of reach of children.

If swallowed, get medical help or contact a Poison Control Center right away.

Directions

- apply liberally 15 minutes before sun exposure
- Use a water resistant sunscreen if swimming or sweating
- Reapply at least every 2 hours
- Children under 6 months of age: Ask a doctor

Sun Protection MeasuresSpending time in the sun increases your risk of skin cancer and early skin aging. To decrease this risk, regularly use a sunscreen with a Broad Spectrum SPF value of 15 or higher and other sun protection measures including:

- limit time in the sun, especially from 10a.m.-2p.m.
- wear long sleeved shirts, pants hats, and sunglasses.

Inactive Ingredients:

Petrolatum, Mineral Oil, Paraffin Wax, Ozokerite Wax, Coconut Oil, Tocopherol, Soybean Oil.

Other Information

Protect this product from excessive heat and direct sun.